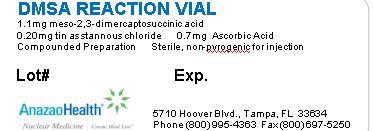 DRUG LABEL: Dimercaptosuccinic Acid
NDC: 51808-211 | Form: INJECTION, POWDER, LYOPHILIZED, FOR SOLUTION
Manufacturer: AnazaoHealth Corporation
Category: prescription | Type: HUMAN PRESCRIPTION DRUG LABEL
Date: 20120701

ACTIVE INGREDIENTS: 2,3-DIMERCAPTOSUCCINIC ACID 1.1 mg/1 1
INACTIVE INGREDIENTS: STANNOUS CHLORIDE 0.20 mg/1 1; ASCORBIC ACID 0.7 mg/1 1

DMSA (Dimercaptosuccinic acid)

Dear Medical Professional,

Per your order, we have compounded DMSA as a sterile freeze-dried mixture. The characteristics of this preparation are:

DESCRIPTION

AnazaoHealth supplies DMSA as a compounded kit for preparing Tc 99m DMSA. Each Reaction vial contains 1.1 mg meso-2, 3-dimercaptosuccinic acid, 0.2 mg tin as stannous chloride, and 0.7 mg ascorbic acid. The vial is back filled with inert gas and may contain a partial vacuum.

Each Acetate buffer vial contains 1.2 ml Sodium Acetate .25 N. pH 5.2 to 5.6.

LDO normal saline included for dilution of prepared kit, if required

CLINICAL PHARMACOLOGY

Technetium Tc 99m DMSA, when administered intravenously apparently binds to plasma proteins in the blood and collects in the renal cortex.

INDICATIONS AND USAGE

Technetium Tc 99m DMSA by intravenous administration is indicated as a static kidney imaging agent.

CONTRAINDICATIONS

There are no known contraindications.

DOSAGE AND ADMINISTRATION

Preparation of Technetium Tc 99m DMSA is done by the following aseptic procedure:

1. Waterproof gloves should be worn during the preparation
2. Snap off the plastic lid and place room temperature reaction vial in an appropriate lead shield.
3. Swab the rubber closure of the vial with a germicide
4. Inject as close to 1 cc as possible of sterile additive free sodium pertechnetate Tc 99m injection containing up to 1480 MBq (40 mCi) into the vial freshly eluded within 2 hours from a technetium generator. Be sure to maintain inert atmosphere in vial by introducing as little air as possible during reconstitution. NOTE: If sodium pertechnetate Tc 99m injection must be diluted, use only Low Dissolved Oxygen (LDO)
5. Secure the lead shield cover. Swirl the vial gently to mix contents and let stand for 15 minutes. Add 1 ml Acetate buffer at this time. (This will interfere with the tagging process if introduced any earlier). Buffer must be added (May be added up to 1 hour after Tc 99m)
6. Examine vial contents; if the solution is not clear and free of particulate matter and discoloration on visual inspection, it should not be used
7. Measure the radioactivity by a suitable calibration system and record prior to patient administration
8. Buffered material should be used within 2 hours
9. Appropriate quality control is recommended

Tagging Tips

- If you need only a one or two mCi dose for your patient, use about 10 mCi of Tc 99m for your kit. Do not stretch your kit to 40 mCi if you do not need to. We have tested the kits to 40 mCi with a Friday generator eluted on Monday but recommend using only what you need
- Keep your volumes low. Take your Tc 99m and dilute to about 1cc with the Low Dissolved Oxygen saline and inject into the DMSA kit
- Let the kit stand for about 15 minutes with just the Tc 99m and DMSA (NO BUFFER)
- After 15 minutes, then add the buffer. This is only for patient comfort and will interfere with the tagging process if introduced any earlier
- After buffering you can add additional “Low Dissolved Oxygen” saline to dilute the kit
- You should inject the dose within 2 hours after making the kit for best results

Storage and Handling

Store the kit at 2°-8°C (36°-46°F) and protect from light

PACKAGE LABEL.PRINCIPAL DISPLAY PANEL

Figure 1